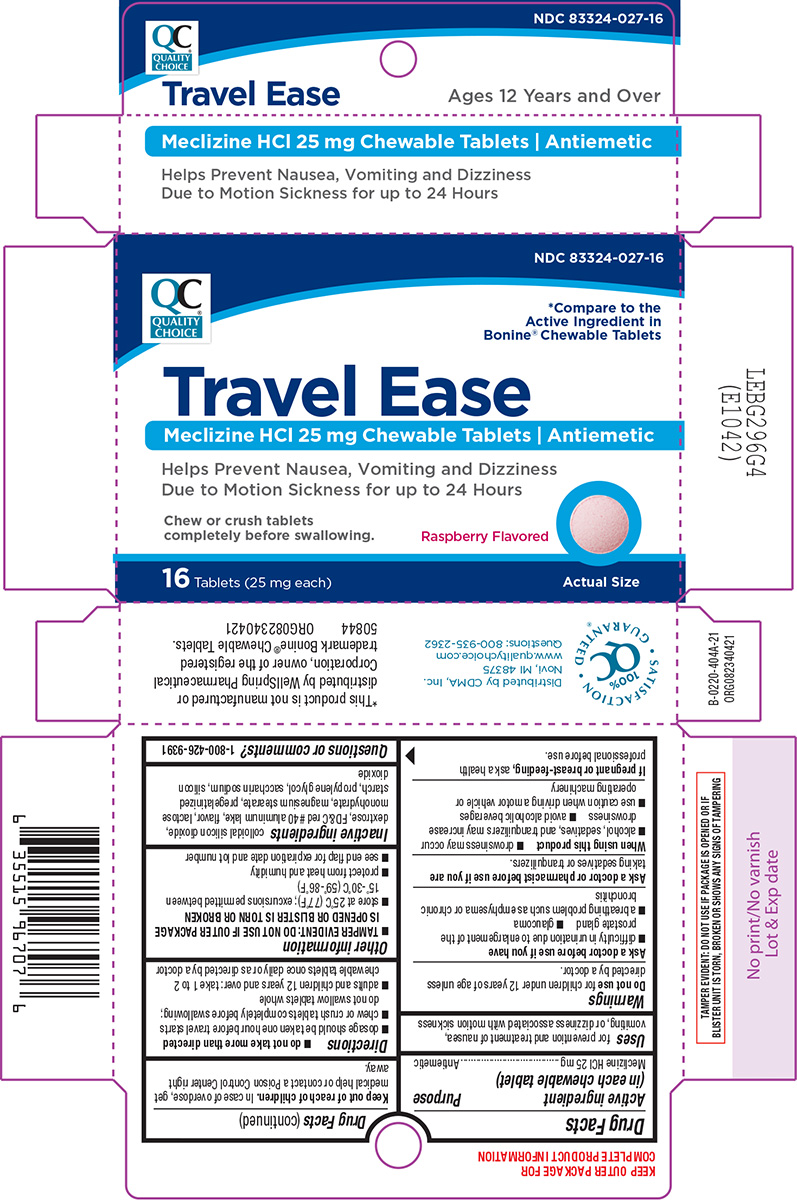 DRUG LABEL: Travel ease
NDC: 83324-027 | Form: TABLET, CHEWABLE
Manufacturer: Chain Drug Marketing Association, Inc.
Category: otc | Type: HUMAN OTC DRUG LABEL
Date: 20250307

ACTIVE INGREDIENTS: MECLIZINE HYDROCHLORIDE 25 mg/1 1
INACTIVE INGREDIENTS: SILICON DIOXIDE; DEXTROSE, UNSPECIFIED FORM; FD&C RED NO. 40 ALUMINUM LAKE; LACTOSE MONOHYDRATE; MAGNESIUM STEARATE; STARCH, CORN; PROPYLENE GLYCOL; SACCHARIN SODIUM

Quality Choice 44-404A

Active ingredient (in each chewable tablet)

Meclizine HCl 25 mg

Purpose

Antiemetic

Uses

for prevention and treatment of nausea, vomiting, or dizziness associated with motion sickness

Warnings

Do not use

for children under 12 years of age unless directed by a doctor.

Ask a doctor before use if you have

- glaucoma
- difficulty in urination due to enlargement of the prostate gland
- a breathing problem such as emphysema or chronic bronchitis

Ask a doctor or pharmacist before use if you are

taking sedatives or tranquilizers.

When using this product

- drowsiness may occur
- alcohol, sedatives, and tranquilizers may increase drowsiness
- avoid alcoholic beverages
- use caution when driving a motor vehicle or operating machinery

If pregnant or breast-feeding,

ask a health professional before use.

Keep out of reach of children.

In case of overdose, get medical help or contact a Poison Control Center right away.

Directions

- do not take more than directed
- dosage should be taken one hour before travel starts
- chew or crush tablets completely before swallowing; do not swallow tablets whole
- adults and children 12 years and over: take 1 to 2 chewable tablets once daily or as directed by a doctor

Other information

- TAMPER EVIDENT: DO NOT USE IF OUTER PACKAGE IS OPENED OR BLISTER IS TORN OR BROKEN
- store at 25ºC (77ºF); excursions permitted between 15º-30ºC (59º-86ºF)
- protect from heat and humidity
- see end flap for expiration date and lot number

Inactive ingredients

colloidal silicon dioxide, dextrose, FD&C red #40 aluminum lake, flavor, lactose monohydrate, magnesium stearate, pregelatinized starch, propylene glycol, saccharin sodium, silicon dioxide

Questions or comments?

1-800-426-9391

Principal Display Panel

NDC 83324-027-16

QC®
QUALITY
CHOICE

*Compare to the
Active Ingredient in
Bonine® Chewable Tablets

Travel Ease
Meclizine HCl 25 mg Chewable Tablets | Antiemetic

Helps Prevent Nausea, Vomiting and Dizziness
Due to Motion Sickness for up to 24 Hours

Chew or crush tablets
completely before swallowing.

Raspberry Flavored

16 Tablets (25 mg each)

Actual Size

TAMPER EVIDENT: DO NOT USE IF PACKAGE IS OPENED OR IF
BLISTER UNIT IS TORN, BROKEN OR SHOWS ANY SIGNS OF TAMPERING

• SATISFACTION
100%
QC®
GUARATNTEED •

Distributed by CDMA, Inc.
Novi, MI 48375
www.qualitychoice.com
Questions: 800-935-2362

*This product is not manufactured or
distributed by WellSpring Pharmaceutical
Corporation, owner of the registered
trademark Bonine® Chewable Tablets.

50844 ORG082340421

Quality choice 44-404A